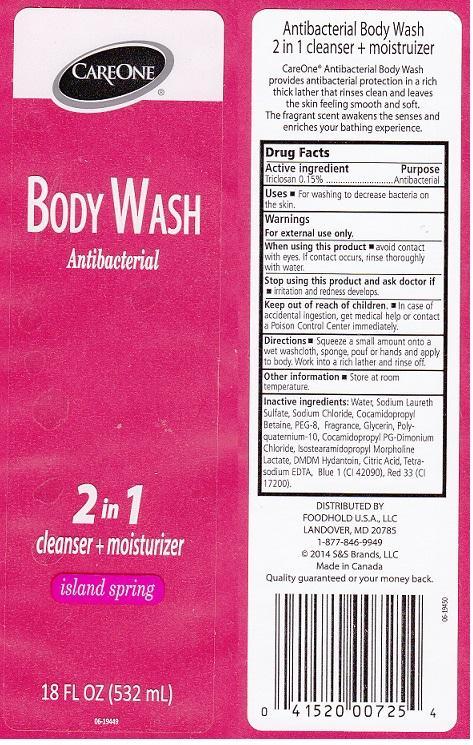 DRUG LABEL: CAREONE
NDC: 41520-807 | Form: LIQUID
Manufacturer: AMERICAN SALES COMPANY
Category: otc | Type: HUMAN OTC DRUG LABEL
Date: 20140324

ACTIVE INGREDIENTS: TRICLOSAN 1.5 mg/1 mL
INACTIVE INGREDIENTS: WATER; SODIUM LAURETH SULFATE; SODIUM CHLORIDE; COCAMIDOPROPYL BETAINE; POLYETHYLENE GLYCOL 400; GLYCERIN; POLYQUATERNIUM-10 (400 CPS AT 2%); COCAMIDOPROPYL PG-DIMONIUM CHLORIDE; ISOSTEARAMIDOPROPYL MORPHOLINE LACTATE; DMDM HYDANTOIN; CITRIC ACID MONOHYDRATE; EDETATE SODIUM; FD&C BLUE NO. 1; D&C RED NO. 33

DRUG FACTS

ACTIVE INGREDIENT

TRICLOSAN 0.15%

PURPOSE

ANTIBACTERIAL

USES

FOR WASHING TO DECREASE BACTERIA ON THE SKIN

WARNINGS

FOR EXTERNAL USE ONLY

WHEN USING THIS PRODUCT

AVOID CONTACT WITH EYES. IF CONTACT OCCURS, RINSE THOROUGHLY WITH WATER

STOP USING THIS PRODUCT AND ASK DOCTOR IF

IRRITATION AND REDNESS DEVELOPS

KEEP OUT OF REACH OF CHILDREN

IN CASE OF ACCIDENTAL INGESTION, GET MEDICAL HELP OR CONTACT A POISON CONTROL CENTER IMMEDIATELY

DIRECTIONS

SQUEEZE A SMALL AMOUNT ONTO A WET WASHCLOTH, SPONGE POUF OR HANDS AND APPLY TO BODY. WORK INTO A RICH LATHER AND RINSE OFF

OTHER INFORMATION

STORE AT ROOM TEMPERATURE

INACTIVE INGREDIENTS

WATER, SODIUM LAURETH SULFATE, SODIUM CHLORIDE, COCAMIDOPROPYL BETAINE, PEG-8, FRAGRANCE, GLYCERIN, POLYQUATERNIUM-10, COCAMIDOPROPYL PG-DIMONIUM CHLORIDE, ISOSTEARAMIDOPROPYL MORPHOLINE LACTATE, DMD HYDANTOIN, CITRIC ACID, TETRASODIUM EDTA, BLUE 1 (CI 42090), RED 33 (CI 17200)